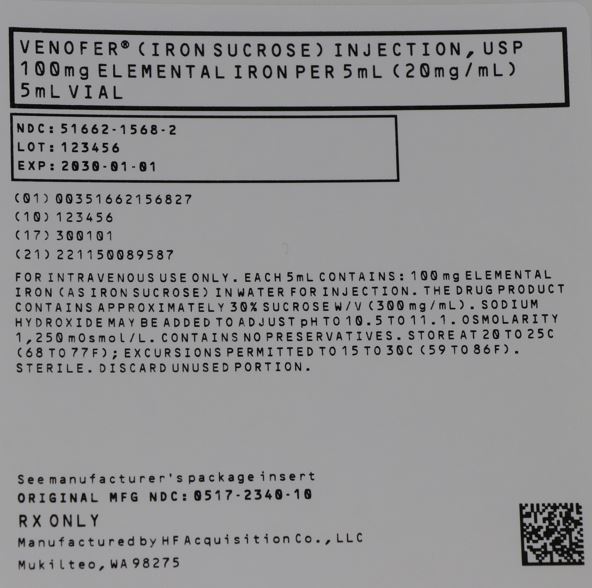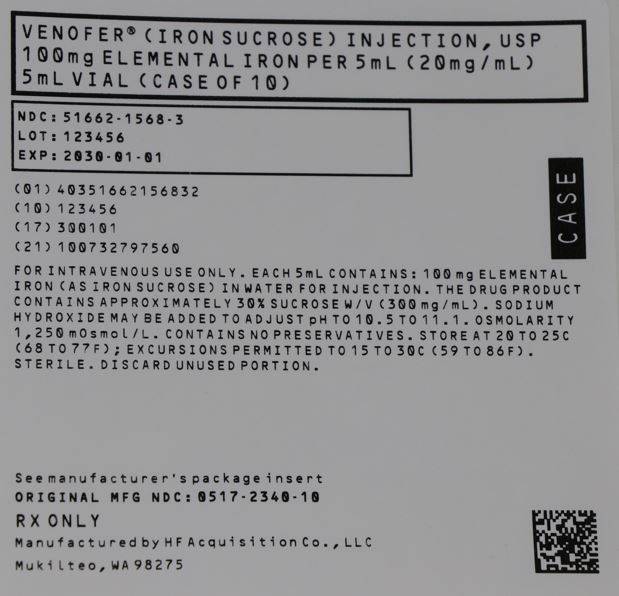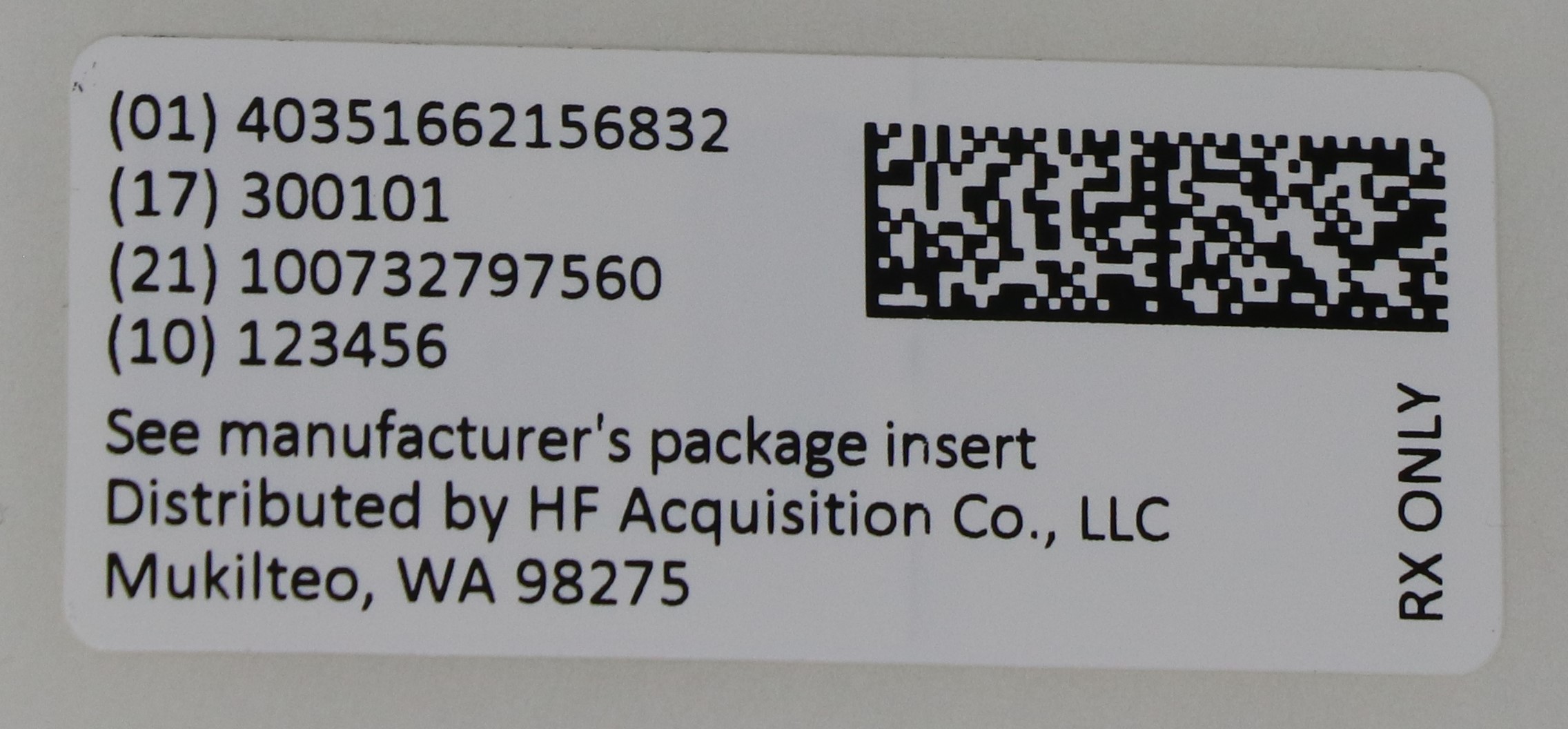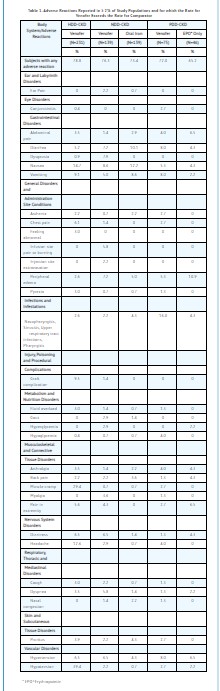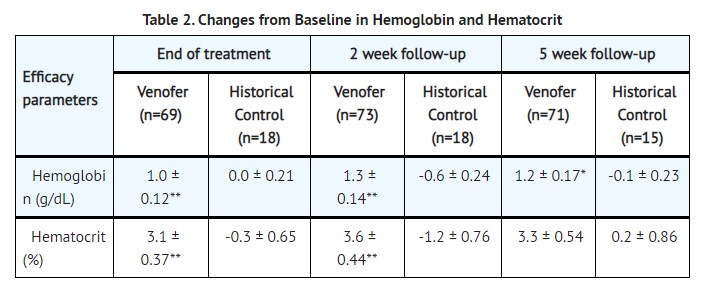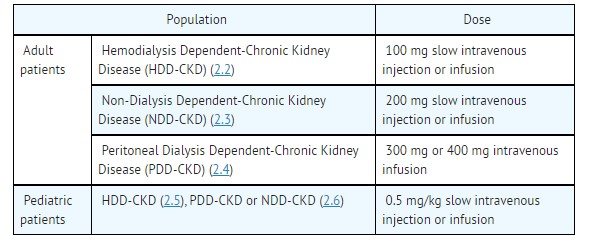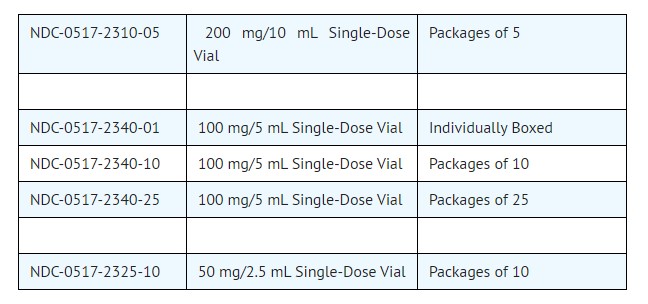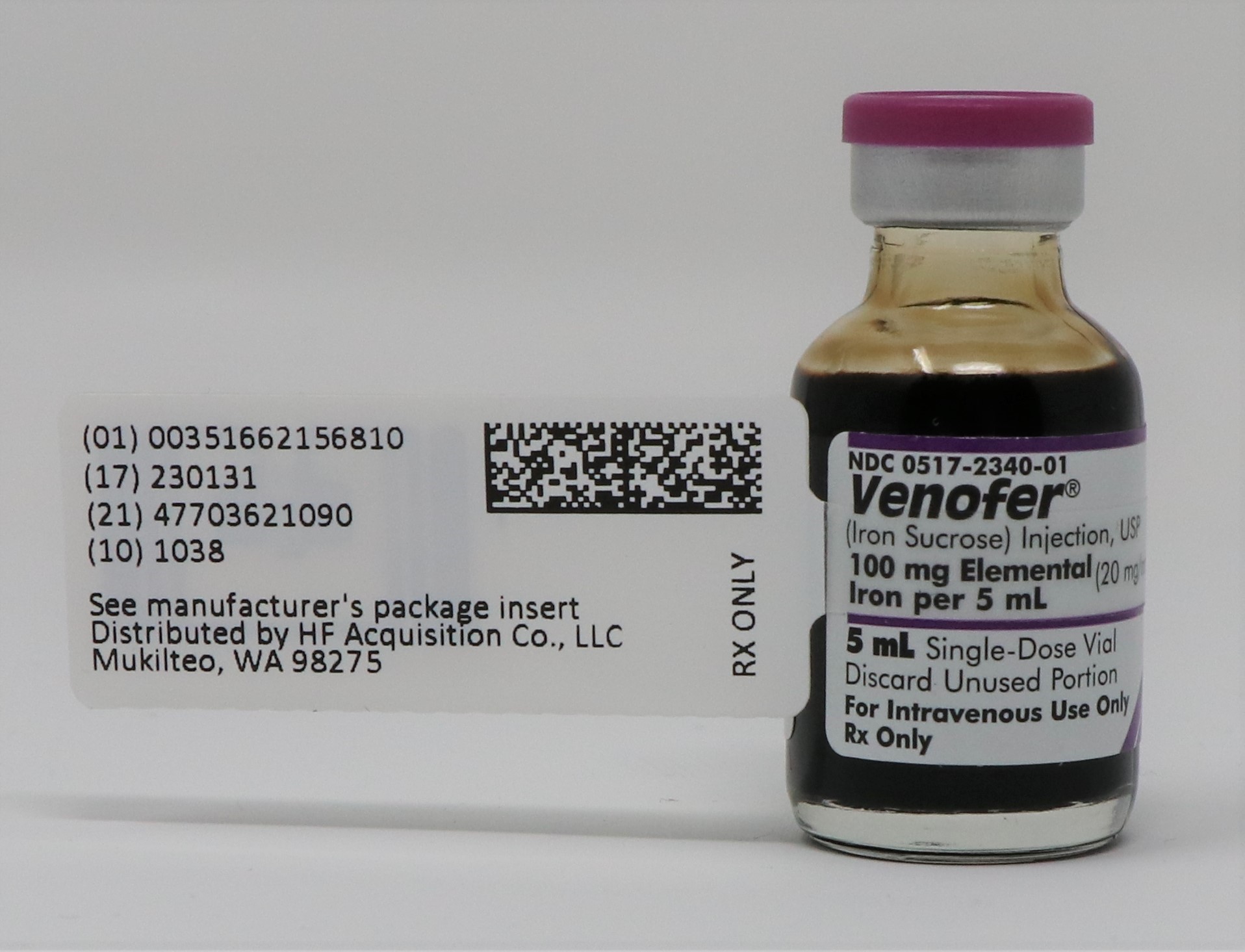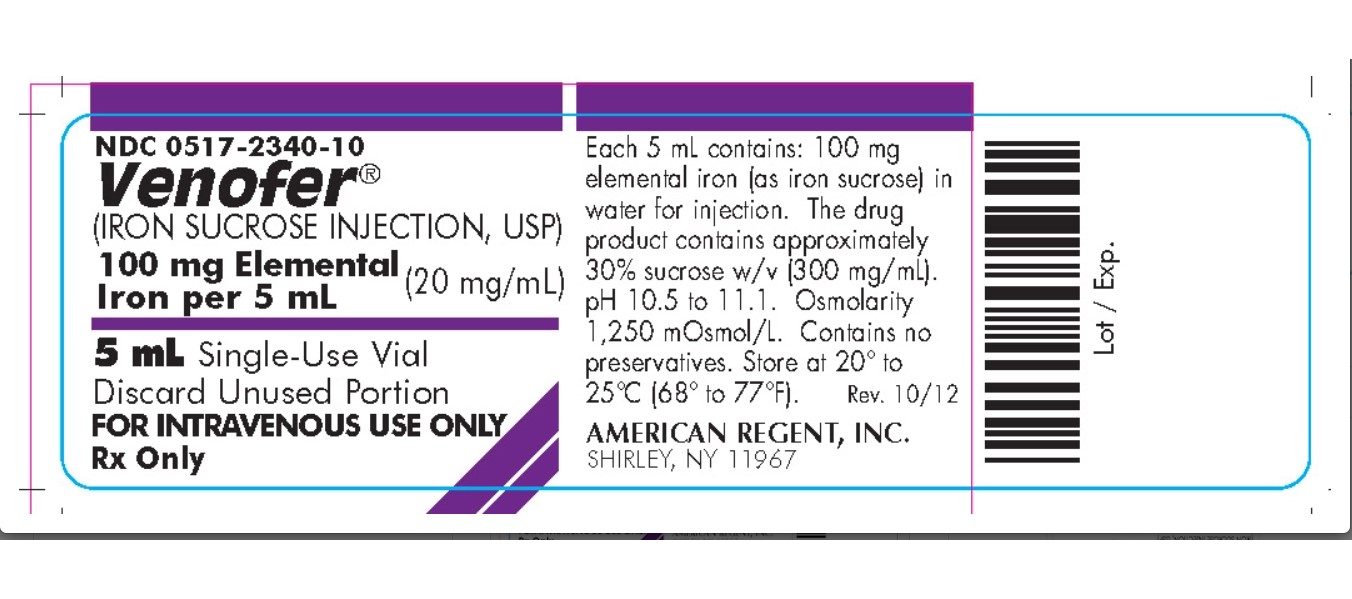 DRUG LABEL: VENOFER (IRON SUCROSE)
NDC: 51662-1568 | Form: INJECTION, SOLUTION
Manufacturer: HF Acquisition Co LLC, DBA HealthFirst
Category: prescription | Type: HUMAN PRESCRIPTION DRUG LABEL
Date: 20240419

ACTIVE INGREDIENTS: IRON SUCROSE 20 mg/1 mL
INACTIVE INGREDIENTS: WATER

VENOFER (IRON SUCROSE INJECTION,USP) 100mg ELEMENTAL IRON PER 5mL (20mg/mL)

HIGHLIGHTS OF PRESCRIBING INFORMATION

These highlights do not include all the information needed to use
VENOFER ® safely and effectively. See full prescribing information for VENOFER.
Venofer (iron sucrose) injection, for intravenous use
Initial U.S. Approval: 2000

INDICATIONS AND USAGE

Venofer is an iron replacement product indicated for the treatment of iron deficiency anemia (IDA) in patients with chronic kidney disease (CKD). (1)

DOSAGE AND ADMINISTRATION

DOSAGE FORMS AND STRENGTHS

Injection: 50 mg/2.5 mL, 100 mg/5 mL, or 200 mg/10 mL (20 mg/mL) in single-dose vials. (3)

CONTRAINDICATIONS

Known hypersensitivity to Venofer (4)

WARNINGS AND PRECAUTIONS

Hypersensitivity Reactions: Observe for signs and symptoms of hypersensitivity during and after Venofer administration for at least 30 minutes and until clinically stable following completion of each administration. Only administer Venofer when personnel and therapies are immediately available for the treatment of serious hypersensitivity reactions. (5.1)
Hypotension: May cause hypotension. Monitor for signs and symptoms of hypotension during and following each administration. (5.2)
Iron Overload: Regularly monitor hematologic responses during therapy. Do not administer to patients with iron overload. (5.3)

ADVERSE REACTIONS

Adult patients: The most common adverse reactions (≥2%) are diarrhea, nausea, vomiting, headache, dizziness, hypotension, pruritus, pain in extremity, arthralgia, back pain, muscle cramp, injection site reactions, chest pain, and peripheral edema. (6.1)
Pediatric patients: The most common adverse reactions (≥2%) are headache, respiratory tract viral infection, peritonitis, vomiting, pyrexia, dizziness, cough, nausea, arteriovenous fistula thrombosis, hypotension, and hypertension. (6.1)

To report SUSPECTED ADVERSE REACTIONS, contact American Regent, Inc. at 1-800-734-9236 or FDA at 1-800-FDA-1088 or www.fda.gov/medwatch.

See 17 for PATIENT COUNSELING INFORMATION.

Revised: 10/2020

TABLE OF CONTENTS

FULL PRESCRIBING INFORMATION: CONTENTS*
1 INDICATIONS AND USAGE
2 DOSAGE AND ADMINISTRATION
2.1 Mode of Administration
2.2 Adult Patients with Hemodialysis Dependent-Chronic Kidney Disease (HDD-CKD)
2.3 Adult Patients with Non-Dialysis Dependent-Chronic Kidney Disease (NDD-CKD)
2.4 Adult Patients with Peritoneal Dialysis Dependent-Chronic Kidney Disease (PDD-CKD)
2.5 Pediatric Patients (2 Years of Age and Older) with HDD-CKD for Iron Maintenance Treatment
2.6 Pediatric Patients (2 Years of Age and Older) with NDD-CKD or PDD-CKD who are on Erythropoietin Therapy for Iron Maintenance Treatment
3 DOSAGE FORMS AND STRENGTHS
4 CONTRAINDICATIONS
5 WARNINGS AND PRECAUTIONS
5.1 Hypersensitivity Reactions
5.2 Hypotension
5.3 Iron Overload
6 ADVERSE REACTIONS
6.1 Adverse Reactions in Clinical Trials
6.2 Adverse Reactions from Post-Marketing Experience
7 DRUG INTERACTIONS
8 USE IN SPECIFIC POPULATIONS
8.1 Pregnancy
8.2 Lactation
8.4 Pediatric Use
8.5 Geriatric Use
10 OVERDOSAGE
11 DESCRIPTION
12 CLINICAL PHARMACOLOGY
12.1 Mechanism of Action
12.2 Pharmacodynamics
12.3 Pharmacokinetics
13 NONCLINICAL TOXICOLOGY
13.1 Carcinogenesis, Mutagenesis, Impairment of Fertility
14 CLINICAL STUDIES
14.1 Clinical Studies Overview
14.2 Study A: Hemodialysis Dependent-Chronic Kidney Disease (HDD–CKD)
14.3 Study B: Hemodialysis Dependent-Chronic Kidney Disease (HDD-CKD)
14.4 Study C: Hemodialysis Dependent-Chronic Kidney Disease (HDD-CKD)
14.5 Study D: Non-Dialysis Dependent-Chronic Kidney Disease (NDD-CKD)
14.6 Study E: Peritoneal Dialysis Dependent-Chronic Kidney Disease (PDD-CKD)
14.7 Study F: Iron Maintenance Treatment Dosing in Pediatric Patients Ages 2 Years and Older with Chronic Kidney Disease
16 HOW SUPPLIED/STORAGE AND HANDLING
16.1 How Supplied
16.2 Stability and Storage 17 PATIENT COUNSELING INFORMATION

*
Sections or subsections omitted from the full prescribing information are not listed.

1 INDICATIONS & USAGE

Venofer is indicated for the treatment of iron deficiency anemia (IDA) in patients with chronic kidney disease (CKD).

2 DOSAGE & ADMINISTRATION

Venofer must only be administered intravenously either by slow injection or by infusion. The dosage of Venofer is expressed in mg of elemental iron. Each mL contains 20 mg of elemental iron.

2.1 Mode of Administration

Administer Venofer only intravenously by slow injection or by infusion. The dosage of Venofer is expressed in mg of elemental iron. Each mL contains 20 mg of elemental iron.

2.2 Adult Patients with Hemodialysis Dependent-Chronic Kidney Disease (HDD-CKD)

Administer Venofer 100 mg undiluted as a slow intravenous injection over 2 to 5 minutes, or as an infusion of 100 mg diluted in a maximum of 100 mL of 0.9% NaCl over a period of at least 15 minutes, per consecutive hemodialysis session [see How Supplied/Storage and Handling (16.2).] Administer Venofer early during the dialysis session (generally within the first hour). The usual total treatment course of Venofer is 1000 mg. Venofer treatment may be repeated if iron deficiency reoccurs.

2.3 Adult Patients with Non-Dialysis Dependent-Chronic Kidney Disease (NDD-CKD)

Administer Venofer 200 mg undiluted as a slow intravenous injection over 2 to 5 minutes or as an infusion of 200 mg in a maximum of 100 mL of 0.9% NaCl over a period of 15 minutes. Administer on 5 different occasions over a 14 day period. There is limited experience with administration of an infusion of 500 mg of Venofer, diluted in a maximum of 250 mL of 0.9% NaCl, over a period of 3.5 to 4 hours on Day 1 and Day 14 [see How Supplied/Storage and Handling (16.2).]Venofer treatment may be repeated if iron deficiency reoccurs.

2.4 Adult Patients with Peritoneal Dialysis Dependent-Chronic Kidney Disease (PDD-CKD)

Administer Venofer in 3 divided doses, given by slow intravenous infusion, within a 28 day period: 2 infusions each of 300 mg over 1.5 hours 14 days apart followed by one 400 mg infusion over 2.5 hours 14 days later. Dilute Venofer in a maximum of 250 mL of 0.9% NaCl [see How Supplied/Storage and Handling (16.2).] Venofer treatment may be repeated if iron deficiency reoccurs.

2.5 Pediatric Patients (2 Years of Age and Older) with HDD-CKD for Iron Maintenance Treatment

For iron maintenance treatment: Administer Venofer at a dose of 0.5 mg/kg, not to exceed 100 mg per dose, every two weeks for 12 weeks given undiluted by slow intravenous injection over 5 minutes or diluted in 0.9% NaCl at a concentration of 1 to 2 mg/mL and administered over 5 to 60 minutes. Do not dilute to concentrations below 1 mg/mL [see How Supplied/Storage and Handling [ 16.2].) Venofer treatment may be repeated if necessary.
The dosing for iron replacement treatment in pediatric patients with HDD-CKD has not been established.

2.6 Pediatric Patients (2 Years of Age and Older) with NDD-CKD or PDD-CKD who are on Erythropoietin Therapy for Iron Maintenance Treatment

For iron maintenance treatment: Administer Venofer at a dose of 0.5 mg/kg, not to exceed 100 mg per dose, every four weeks for 12 weeks given undiluted by slow intravenous injection over 5 minutes or diluted in 0.9% NaCl at a concentration of 1 to 2 mg/mL and administered over 5 to 60 minutes. Do not dilute to concentrations below 1 mg/mL [see How Supplied/Storage and Handling (16.2).] Venofer treatment may be repeated if necessary.
The dosing for iron replacement treatment in pediatric patients with NDD-CKD or PDD-CKD has not been established.

3 DOSAGE FORMS & STRENGTHS

Injection: 50 mg/2.5 mL, 100 mg/5 mL, or 200 mg/10 mL (20 mg/mL) in single-dose vials. (3)

4 CONTRAINDICATIONS

Known hypersensitivity to Venofer.

5 WARNINGS AND PRECAUTIONS

5.1 Hypersensitivity Reactions

Serious hypersensitivity reactions, including anaphylactic-type reactions, some of which have been life-threatening and fatal, have been reported in patients receiving Venofer. Patients may present with shock, clinically significant hypotension, loss of consciousness, and/or collapse. If hypersensitivity reactions or signs of intolerance occur during administration, stop Venofer immediately. Monitor patients for signs and symptoms of hypersensitivity during and after Venofer administration for at least 30 minutes and until clinically stable following completion of the infusion. Only administer Venofer when personnel and therapies are immediately available for the treatment of serious hypersensitivity reactions. Most reactions associated with intravenous iron preparations occur within 30 minutes of the completion of the infusion [see Adverse Reactions (6.1 and 6.2)].

5.2 Hypotension

Venofer may cause clinically significant hypotension. Monitor for signs and symptoms of hypotension following each administration of Venofer. Hypotension following administration of Venofer may be related to the rate of administration and/or total dose administered [see Dosage and Administration (2), Warnings and Precautions (5.1), and Adverse Reactions (6.2)].

5.3 Iron Overload

Excessive therapy with parenteral iron can lead to excess storage of iron with the possibility of iatrogenic hemosiderosis. All adult and pediatric patients receiving Venofer require periodic monitoring of hematologic and iron parameters (hemoglobin, hematocrit, serum ferritin and transferrin saturation). Do not administer Venofer to patients with evidence of iron overload. Transferrin saturation (TSAT) values increase rapidly after intravenous administration of iron sucrose; do not perform serum iron measurements for at least 48 hours after intravenous dosing [see Dosage and Administration (2) and Overdosage (10)].

6 ADVERSE REACTIONS

The following clinically significant adverse reactions are described elsewhere in the labeling:

Hypersensitivity Reactions [see Warnings and Precautions (5.1)]

Hypotension [see Warnings and Precautions (5.2)]

Iron Overload [see Warnings and Precautions (5.3)]

6.1 Adverse Reactions in Clinical Trials

Because clinical trials are conducted under widely varying conditions, adverse reaction rates observed in the clinical trials of a drug may not reflect the rates observed in practice.

Adverse Reactions in Adults Patients with CKD

The frequency of adverse reactions associated with the use of Venofer has been documented in six clinical trials involving 231 patients with HDD-CKD, 139 patients with NDD-CKD and 75 patients with PDD-CKD. Adverse reactions reported by ≥ 2% of treated patients in the six clinical trials for which the rate for Venofer exceeds the rate for comparator are listed by indication in Table 1. Patients with HDD-CKD received 100 mg doses at 10 consecutive dialysis sessions until a cumulative dose of 1000 mg was administered. Patients with NDD-CKD received either 5 doses of 200 mg over 2 weeks or 2 doses of 500 mg separated by fourteen days, and patients with PDD-CKD received 2 doses of 300 mg followed by a dose of 400 mg over a period of 4 weeks.

One hundred thirty (11%) of the 1,151 patients evaluated in the 4 U.S. trials in HDD-CKD patients (studies A, B and the two post marketing studies) had prior other intravenous iron therapy and were reported to be intolerant (defined as precluding further use of that iron product). When these patients were treated with Venofer there were no occurrences of adverse reactions that precluded further use of Venofer [see Warning and Precautions (5)].

Adverse Reactions in Pediatric Patients with CKD (ages 2 years and older)

In a randomized, open-label, dose-ranging trial for iron maintenance treatment with Venofer in pediatric patients with CKD on stable erythropoietin therapy [see Clinical Studies (14.7)], at least one adverse reaction was experienced by 57% (27/47) of the patients receiving Venofer 0.5 mg/kg, 53% (25/47) of the patients receiving Venofer 1 mg/kg, and 55% (26/47) of the patients receiving Venofer 2 mg/kg.

A total of 5 (11%) subjects in the Venofer 0.5 mg/kg group, 10 (21%) patients in the Venofer 1 mg/kg group, and 10 (21%) patients in the Venofer 2 mg/kg group experienced at least 1 serious adverse reaction during the study. The most common adverse reactions (>2% of patients) in all patients were headache (6%), respiratory tract viral infection (4%), peritonitis (4%), vomiting (4%), pyrexia (4%), dizziness (4%), cough (4%), nausea (3%), arteriovenous fistula thrombosis (2%), hypotension (2%), and hypertension (2.1%).

6.2 Adverse Reactions from Post-Marketing Experience

The following adverse reactions have been identified during post-approval use of Venofer. Because these reactions are reported voluntarily from a population of uncertain size, it is not always possible to reliably estimate their frequency or establish a causal relationship to drug exposure.

In the post-marketing safety studies in 1,051 treated patients with HDD-CKD, the adverse reactions reported by >1% were cardiac failure congestive, sepsis and dysgeusia.

Immune system disorders: anaphylactic-type reactions, angioedema

Psychiatric disorders: confusion

Nervous system disorders: convulsions, collapse, light-headedness, loss-of-consciousness

Cardiac disorders: bradycardia

Vascular disorders: shock

Respiratory, thoracic and mediastinal disorders: bronchospasm, dyspnea

Musculoskeletal and connective tissue disorders: back pain, swelling of the joints

Renal and urinary disorders: chromaturia

General disorders and administration site conditions: hyperhidrosis

Symptoms associated with Venofer total dosage or infusing too rapidly included hypotension, dyspnea, headache, vomiting, nausea, dizziness, joint aches, paresthesia, abdominal and muscle pain, edema, and cardiovascular collapse. These adverse reactions have occurred up to 30 minutes after the administration of Venofer injection. Reactions have occurred following the first dose or subsequent doses of Venofer. Symptoms may respond to intravenous fluids, hydrocortisone, and/or antihistamines. Slowing the infusion rate may alleviate symptoms.

Injection site discoloration has been reported following extravasation. Assure stable intravenous access to avoid extravasation.

7 DRUG INTERACTIONS

Venofer may reduce the absorption of concomitantly administered oral iron preparations.

8 USE IN SPECIFIC POPULATIONS

8.1 Pregnancy

Risk Summary

Published studies on intravenous iron sucrose treatment after the first trimester of pregnancy have not shown adverse maternal or fetal outcomes (see Data). Available reports of intravenous iron sucrose use in pregnant women during the first trimester are insufficient to assess the risk of major birth defects and miscarriage. There are risks to the mother and fetus associated with untreated IDA in pregnancy as well as risks to the fetus associated with maternal severe hypersensitivity reactions (see Clinical Considerations). Animal reproduction studies of iron sucrose administered to rats and rabbits during the period of organogenesis at elemental iron doses equivalent to the maximum recommended human dose based on body surface area revealed no evidence of harm to the fetus (see Data). The estimated background risk of major birth defects and miscarriage for the indicated populations is unknown. Adverse outcomes in pregnancy occur regardless of the health of the mother or the use of medications. In the U.S. general population, the estimated background risk of major birth defects and miscarriage in clinically-recognized pregnancies is 2-4% and 15-20%, respectively.

Clinical Considerations

Disease-associated maternal and/or embryo/fetal risk

Iron deficiency anemia during pregnancy should be treated. Untreated IDA in pregnancy is associated with adverse maternal outcomes such as post-partum anemia. Adverse pregnancy outcomes associated with IDA include increased risk for preterm delivery and low birth weight.
Fetal/Neonatal adverse reactions

Severe adverse reactions including circulatory failure (severe hypotension, shock including in the context of anaphylactic reaction) may occur in pregnant women with parenteral iron products (such as Venofer) which may cause fetal bradycardia, especially during the second and third trimester.

Data

Human Data

Published data from randomized controlled studies and prospective observational studies on the use of Venofer in pregnant women have not reported an association of Venofer and adverse developmental outcomes. However, these studies did not include women exposed during the first trimester of pregnancy and were not designed to assess the risk of major birth defects. Maternal adverse events reported in these studies are similar to those reported during clinical trials in adult males and non-pregnant females [seeAdverse Reactions (6.1)].

Animal Data

Iron sucrose was administered intravenously to rats and rabbits during the period of organogenesis at elemental iron doses up to 13 mg/kg/day (0.25 times or equivalent to the maximum recommended human dose based on body surface area, respectively) and revealed no evidence of harm to the fetus.

8.2 Lactation

Risk Summary

Iron sucrose is present in human milk, and available published reports following exposure to 100-300 mg intravenous iron sucrose have not reported adverse reactions in breastfed infants (see Data). There are no data on the effects on milk production. The developmental and health benefits of breastfeeding should be considered, along with the mother’s clinical need for Venofer and any potential adverse effects on the breastfed child from Venofer or from the underlying maternal condition.

Data

A published study showed no difference in iron concentration in the colostrum of 10 iron deficient breastfeeding women who were 2 to 3 days postpartum and received a single dose of 100 mg of intravenous iron sucrose compared to 5 breastfeeding women who received no iron. These results may underestimate the amount of iron in breastmilk following the standard dose of Venofer.

A published report of 78 breastfeeding women who received 300 mg of intravenous iron sucrose over 3 days (infant age not reported) did not report on the safety of iron sucrose in breastfed infants; however adverse reactions in breastfed infants were not reported.

Clinical Considerations

Monitor breastfed infants for gastrointestinal toxicity (constipation, diarrhea).

8.4 Pediatric Use

Safety and effectiveness of Venofer for iron replacement treatment in pediatric patients with dialysis-dependent or non-dialysis-dependent CKD have not been established.

Safety and effectiveness of Venofer for iron maintenance treatment in pediatric patients 2 years of age and older with dialysis-dependent or non-dialysis-dependent CKD receiving erythropoietin therapy were studied. Venofer at doses of 0.5 mg/kg, 1 mg/kg, and 2 mg/kg was administered. All three doses maintained hemoglobin between 10.5 g/dL and 14.0 g/dL in about 50% of subjects over the 12-week treatment period with stable EPO dosing [see Clinical Studies (14.7)].

Venofer has not been studied in patients younger than 2 years of age.

In a country where Venofer is available for use in children, at a single site, five premature infants (weight less than 1,250 g) developed necrotizing enterocolitis and two of the five died during or following a period when they received Venofer, several other medications and erythropoietin. Necrotizing enterocolitis may be a complication of prematurity in very low birth weight infants. No causal relationship to Venofer or any other drugs could be established.

8.5 Geriatric Use

Of the 1,051 patients in two post-marketing safety studies of Venofer, 40% were 65 years and older. No overall differences in safety or effectiveness were observed between these subjects and younger subjects, and other reported clinical experience has not identified differences in responses between the elderly and younger patients, but greater sensitivity of some older individuals cannot be ruled out. In general, dose administration to an elderly patient should be cautious, reflecting the greater frequency of decreased hepatic, renal, or cardiac function, and of concomitant disease or other drug therapy.

10 OVERDOSAGE

No data are available regarding overdosage of Venofer in humans. Excessive dosages of Venofer may lead to accumulation of iron in storage sites potentially leading to hemosiderosis. Do not administer Venofer to patients with iron overload [see Warnings and Precautions (5.3)]. Venofer is not dialyzable through CA210 (Baxter) High Efficiency or Fresenius F80A High Flux dialysis membranes.

Toxicities in single-dose studies in mice and rats, at intravenous iron sucrose doses up to 8 times the maximum recommended human dose based on body surface area, included sedation, hypoactivity, pale eyes, bleeding in the gastrointestinal tract and lungs, and mortality.

11 DESCRIPTION

Venofer (iron sucrose injection, USP), an iron replacement product, is a brown, sterile, aqueous, complex of polynuclear iron (III)-hydroxide in sucrose for intravenous use. Iron sucrose injection has a molecular weight of approximately 34,000 to 60,000 daltons and a proposed structural formula:

[Na2Fe5O8(OH) ·3(H2O)]n ·m(C12H22O11)

where: n is the degree of iron polymerization and m is the number of sucrose molecules associated with the iron (III)-hydroxide.

Each mL contains 20 mg elemental iron as iron sucrose in water for injection. Venofer is available in 10 mL single-dose vials (200 mg elemental iron per 10 mL), 5 mL single-dose vials (100 mg elemental iron per 5 mL), and 2.5 mL single-dose vials (50 mg elemental iron per 2.5 mL). The drug product contains approximately 30% sucrose w/v (300 mg/mL). Sodium hydroxide may be added to adjust pH to 10.5 to 11.1. The product contains no preservatives. The osmolarity of the injection is 1,250 mOsmol/L.

12 CLINICAL PHARMACOLOGY

12.1 Mechanism of Action

Venofer is an aqueous complex of poly-nuclear iron (III)-hydroxide in sucrose. Following intravenous administration, Venofer is dissociated into iron and sucrose and the iron is transported as a complex with transferrin to target cells including erythroid precursor cells. The iron in the precursor cells is incorporated into hemoglobin as the cells mature into red blood cells.

12.2 Pharmacodynamics

Following intravenous administration, Venofer is dissociated into iron and sucrose. In 22 patients undergoing hemodialysis and receiving erythropoietin (recombinant human erythropoietin) therapy treated with iron sucrose containing 100 mg of iron, three times weekly for three weeks, significant increases in serum iron and serum ferritin and significant decreases in total iron binding capacity occurred four weeks from the initiation of iron sucrose treatment.

12.3 Pharmacokinetics

In healthy adults administered intravenous doses of Venofer, its iron component exhibited first order kinetics with an elimination half-life of 6 h, total clearance of 1.2 L/h, and steady state apparent volume of distribution of 7.9 L. The iron component appeared to distribute mainly in blood and to some extent in extravascular fluid. A study evaluating Venofer containing 100 mg of iron labeled with 52Fe/59Fe in patients with iron deficiency showed that a significant amount of the administered iron is distributed to the liver, spleen and bone marrow and that the bone marrow is an irreversible iron trapping compartment.

Following intravenous administration of Venofer, iron sucrose is dissociated into iron and sucrose. The sucrose component is eliminated mainly by urinary excretion. In a study evaluating a single intravenous dose of Venofer containing 1,510 mg of sucrose and 100 mg of iron in 12 healthy adults (9 female, 3 male: age range 32 to 52), 68.3% of the sucrose was eliminated in urine in 4 h and 75.4% in 24 h. Some iron was also eliminated in the urine. Neither transferrin nor transferrin receptor levels changed immediately after the dose administration. In this study and another study evaluating a single intravenous dose of iron sucrose containing 500 to 700 mg of iron in 26 patients with anemia on erythropoietin therapy (23 female, 3 male; age range 16 to 60), approximately 5% of the iron was eliminated in urine in 24 h at each dose level. The effects of age and gender on the pharmacokinetics of Venofer have not been studied.

Pharmacokinetics in Pediatric Patients

In a single-dose PK study of Venofer, patients with NDD-CKD ages 12 to 16 (N=11) received intravenous bolus doses of Venofer at 7 mg/kg (maximum 200 mg) administered over 5 minutes. Following a single dose of Venofer, the half-life of total serum iron was 8 hours. The mean Cmax and AUC values were 8545 μg/dl and 31305 hr•μg/dL, respectively, which were 1.42- and 1.67-fold higher than dose adjusted adult Cmax and AUC values.

Venofer is not dialyzable through CA210 (Baxter) High Efficiency or Fresenius F80A High Flux dialysis membranes. In in vitro studies, the amount of iron sucrose in the dialysate fluid was below the levels of detection of the assay (less than 2 parts per million).

13 NONCLINICAL TOXICOLOGY

13.1 Carcinogenesis, Mutagenesis, Impairment of Fertility

Carcinogenicity studies have not been performed with iron sucrose.

Iron sucrose was not mutagenic in vitro in the bacterial reverse mutation assay (Ames test) or the mouse lymphoma assay. Iron sucrose was not clastogenic in the in vitro chromosome aberration assay using human lymphocytes or in the in vivo mouse micronucleus assay.

Iron sucrose at intravenous doses up to 15 mg/kg/day of elemental iron (1.2 times the maximum recommended human dose based on body surface area) had no effect on fertility and reproductive function of male and female rats.

14 CLINICAL STUDIES

Five clinical trials involving 647 adult patients and one clinical trial involving 131 pediatric patients were conducted to assess the safety and efficacy of Venofer.

14.1 Clinical Studies Overview

Five clinical trials involving 647 adult patients and one clinical trial involving 131 pediatric patients were conducted to assess the safety and efficacy of Venofer.

14.2 Study A: Hemodialysis Dependent-Chronic Kidney Disease (HDD–CKD)

Study A was a multicenter, open-label, historically-controlled study in 101 patients with HDD-CKD (77 patients with Venofer treatment and 24 in the historical control group) with IDA. Eligibility criteria for Venofer treatment included patients undergoing chronic hemodialysis, receiving erythropoietin, hemoglobin level between 8.0 and 11.0 g/dL, transferrin saturation <20%, and serum ferritin <300 ng/mL. The mean age of the patients was 65 years with the age range of 31 to 85 years. Of the 77 patients, 44 (57%) were male and 33 (43%) were female.

Venofer 100 mg was administered at 10 consecutive dialysis sessions either as slow injection or a slow infusion. The historical control population consisted of 24 patients with similar ferritin levels as patients treated with Venofer, who were off intravenous iron for at least 2 weeks and who had received erythropoietin therapy with hematocrit averaging 31 to 36 for at least two months prior to study entry. The mean age of patients in the historical control group was 56 years, with an age range of 29 to 80 years. Patient age and serum ferritin level were similar between treatment and historical control patients.

Patients in the Venofer treated population showed a greater increase in hemoglobin and hematocrit than did patients in the historical control population. See Table 2.

**p < 0.01 and *p < 0.05 compared to historical control from ANCOVA analysis with baseline hemoglobin, serum ferritin and erythropoietin dose as covariates.

Serum ferritin increased at endpoint of study from baseline in the Venofer-treated population (165.3 ± 24.2 ng/mL) compared to the historical control population (-27.6 ± 9.5 ng/mL). Transferrin saturation also increased at endpoint of study from baseline in the Venofer-treated population (8.8 ± 1.6%) compared to this historical control population (-5.1 ± 4.3%).

14.3 Study B: Hemodialysis Dependent-Chronic Kidney Disease (HDD-CKD)

Study B was a multicenter, open label study of Venofer in 23 patients with iron deficiency and HDD-CKD who had been discontinued from iron dextran due to intolerance. Eligibility criteria were otherwise identical to Study A. The mean age of the patients in this study was 53 years, with ages ranging from 21 to 79 years. Of the 23 patients enrolled in the study, 10 (44%) were male and 13 (56%) were female.

All 23 enrolled patients were evaluated for efficacy. Increases in mean hemoglobin (1.1 ± 0.2 g/dL), hematocrit (3.6 ± 0.6%), serum ferritin (266.3 ± 30.3 ng/mL) and transferrin saturation (8.7 ± 2.0%) were observed from baseline to end of treatment.

14.4 Study C: Hemodialysis Dependent-Chronic Kidney Disease (HDD-CKD)

Study C was a multicenter, open-label study in patients with HDD-CKD. This study enrolled patients with a hemoglobin ≤ 10 g/dL, a serum transferrin saturation ≤ 20%, and a serum ferritin ≤ 200 ng/mL, who were undergoing maintenance hemodialysis 2 to 3 times weekly. The mean age of the patients enrolled in this study was 41 years, with ages ranging from 16 to 70 years. Of 130 patients evaluated for efficacy in this study, 68 (52%) were male and 62 (48%) were female. Forty-eight percent of the patients had previously been treated with oral iron. Exclusion criteria were similar to those in studies A and B. Venofer was administered in doses of 100 mg during sequential dialysis sessions until a pre-determined (calculated) total dose of iron was administered. A 50 mg dose (2.5 mL) was given to patients within two weeks of study entry as a test dose. Twenty-seven patients (20%) were receiving erythropoietin treatment at study entry and they continued to receive the same erythropoietin dose for the duration of the study.

The modified intention-to-treat (mITT) population consisted of 131 patients. Increases from baseline in mean hemoglobin (1.7 g/dL), hematocrit (5%), serum ferritin (434.6 ng/mL), and serum transferrin saturation (14%) were observed at week 2 of the observation period and these values remained increased at week 4 of the observation period.

14.5 Study D: Non-Dialysis Dependent-Chronic Kidney Disease (NDD-CKD)

Study D (NCT00236977) was a randomized, open-label, multicenter, active-controlled study of the safety and efficacy of oral iron versus Venofer in patients with NDD-CKD with or without erythropoietin therapy. Erythropoietin therapy was stable for 8 weeks prior to randomization. In the study 188 patients with NDD-CKD, hemoglobin of ≤ 11.0 g/dL, transferrin saturation ≤ 25%, ferritin ≤ 300 ng/mL were randomized to receive oral iron (325 mg ferrous sulfate three times daily for 56 days); or Venofer (either 200 mg over 2 to 5 minutes 5 times within 14 days or two 500 mg infusions on Day 1 and Day 14, administered over 3.5 to 4 hours). The mean age of the 91 treated patients in the Venofer group was 61.6 years (range 25 to 86 years) and 64 years (range 21 to 86 years) for the 91 patients in the oral iron group.

A statistically significantly greater proportion of Venofer subjects (35/79; 44.3%) compared to oral iron subjects (23/82; 28%) had an increase in hemoglobin ≥ 1 g/dL at anytime during the study (p = 0.03).

14.6 Study E: Peritoneal Dialysis Dependent-Chronic Kidney Disease (PDD-CKD)

Study E (NCT00236938) was a randomized, open-label, multicenter study comparing patients with PDD-CKD receiving an erythropoietin and intravenous iron to patients with PDD-CKD receiving an erythropoietin alone without iron supplementation. Patients with PDD-CKD, stable erythropoietin for 8 weeks, hemoglobin of ≤ 11.5 g/dL, TSAT ≤ 25%, ferritin ≤ 500 ng/mL were randomized to receive either no iron or Venofer (300 mg in 250 mL 0.9% NaCl over 1.5 hours on Day 1 and 15 and 400 mg in 250 mL 0.9% NaCl over 2.5 hours on Day 29). The mean age of the 75 treated patients in the Venofer / erythropoietin group was 51.9 years (range 21 to 81 years) vs. 52.8 years (range 23 to 77 years) for 46 patients in the erythropoietin alone group.

Patients in the Venofer / erythropoietin group had statistically significantly greater mean change from baseline to the highest hemoglobin value (1.3 g/dL), compared to subjects who received erythropoietin alone (0.6 g/dL) (p < 0.01). A greater proportion of subjects treated with Venofer / erythropoietin (59.1 %) had an increase in hemoglobin of ≥ 1 g/dL at any time during the study compared to the subjects who received erythropoietin only (33.3%).

14.7 Study F: Iron Maintenance Treatment Dosing in Pediatric Patients Ages 2 Years and Older with Chronic Kidney Disease

Study F (NCT00239642) was a randomized, open-label, dose-ranging study for iron maintenance treatment in pediatric patients with dialysis-dependent or non-dialysis-dependent CKD on stable erythropoietin therapy. The study randomized patients to one of three doses of Venofer (0.5 mg/kg, 1 mg/kg or 2 mg/kg). The mean age was 13 years (range 2 to 20 years). Over 70% of patients were 12 years or older in all three groups. There were 84 males and 61 females. About 60% of patients underwent hemodialysis and 25% underwent peritoneal dialysis in all three dose groups. At baseline, the mean hemoglobin was 12 g/dL, the mean TSAT was 33% and the mean ferritin was 300 ng/mL. Patients with HDD-CKD received Venofer once every other week for 6 doses. Patients with PDD-CKD or NDD-CKD received Venofer once every 4 weeks for 3 doses. Among 131 evaluable patients with stable erythropoietin dosing, the proportion of patients who maintained hemoglobin between 10.5 g/dL and 14.0 g/dL during the 12-week treatment period was 58.7%, 46.7%, and 45.0% in the Venofer 0.5 mg/kg, 1 mg/kg, and 2 mg/kg groups, respectively. A dose-response relationship was not demonstrated.

16 HOW SUPPLIED/STORAGE AND HANDLING

16.1 How Supplied

Venofer is supplied sterile in 10 mL, 5 mL, and 2.5 mL single-dose vials. Each 10 mL vial contains 200 mg elemental iron, each 5 mL vial contains 100 mg elemental iron, and each 2.5 mL vial contains 50 mg elemental iron (20 mg/mL).

16.2 Stability and Storage

Contains no preservatives. Store in original carton at 20°C to 25°C (68° F to 77° F); excursions permitted to 15° to 30°C (59° to 86°F) [see USP Controlled Room Temperature]. Do not freeze.

Syringe Stability: Venofer, when diluted with 0.9% NaCl at concentrations ranging from 2 mg to 10 mg of elemental iron per mL, or undiluted (20 mg elemental iron per mL) and stored in a plastic syringe, was found to be physically and chemically stable for 7 days at controlled room temperature (25°C ± 2°C) and under refrigeration (4°C ± 2°C).

Intravenous Admixture Stability: Venofer, when added to intravenous infusion bags (PVC or non-PVC) containing 0.9% NaCl at concentrations ranging from 1 mg to 2 mg of elemental iron per mL, has been found to be physically and chemically stable for 7 days at controlled room temperature (25°C ± 2°C).

Do not dilute to concentrations below 1 mg/mL.

Do not mix Venofer with other medications or add to parenteral nutrition solutions for intravenous infusion.

Parenteral drug products should be inspected visually for particulate matter and discoloration prior to infusion.

17 PATIENT COUNSELING INFORMATION

Prior History of Reactions to Parenteral Iron Products
Question patients regarding any prior history of reactions to parenteral iron products [see Warnings and Precautions (5)].

Serious Hypersensitivity Reactions
Advise patients to report any symptoms of hypersensitivity that may develop during and following Venofer administration, such as rash, itching, dizziness, light-headedness, swelling, and breathing problems [see Warnings and Precautions (5)].

AMERICAN
REGENT, INC.
SHIRLEY, NY 11967
Venofer is manufactured under license from Vifor (International) Inc., Switzerland.

IN2340
MG #15727